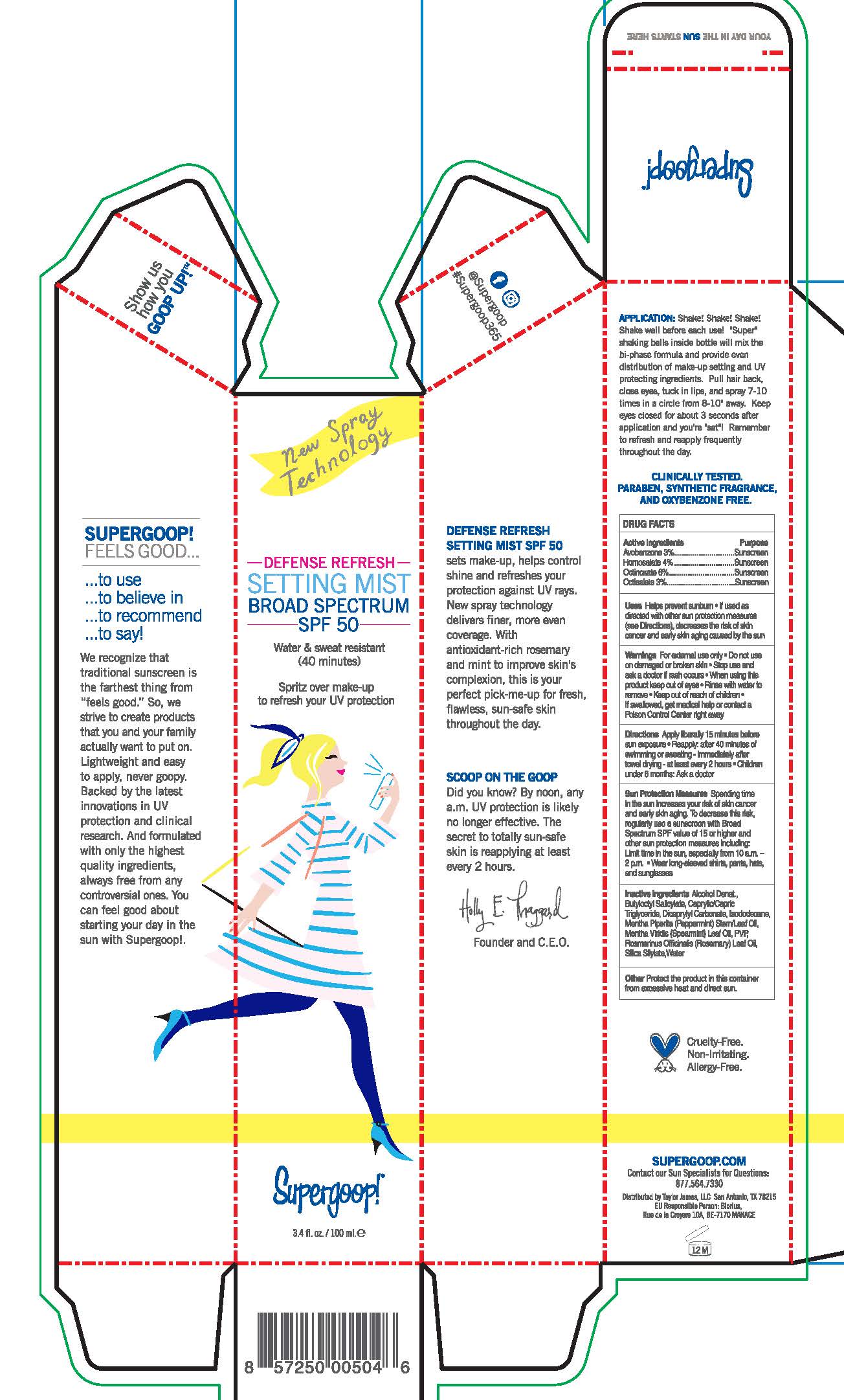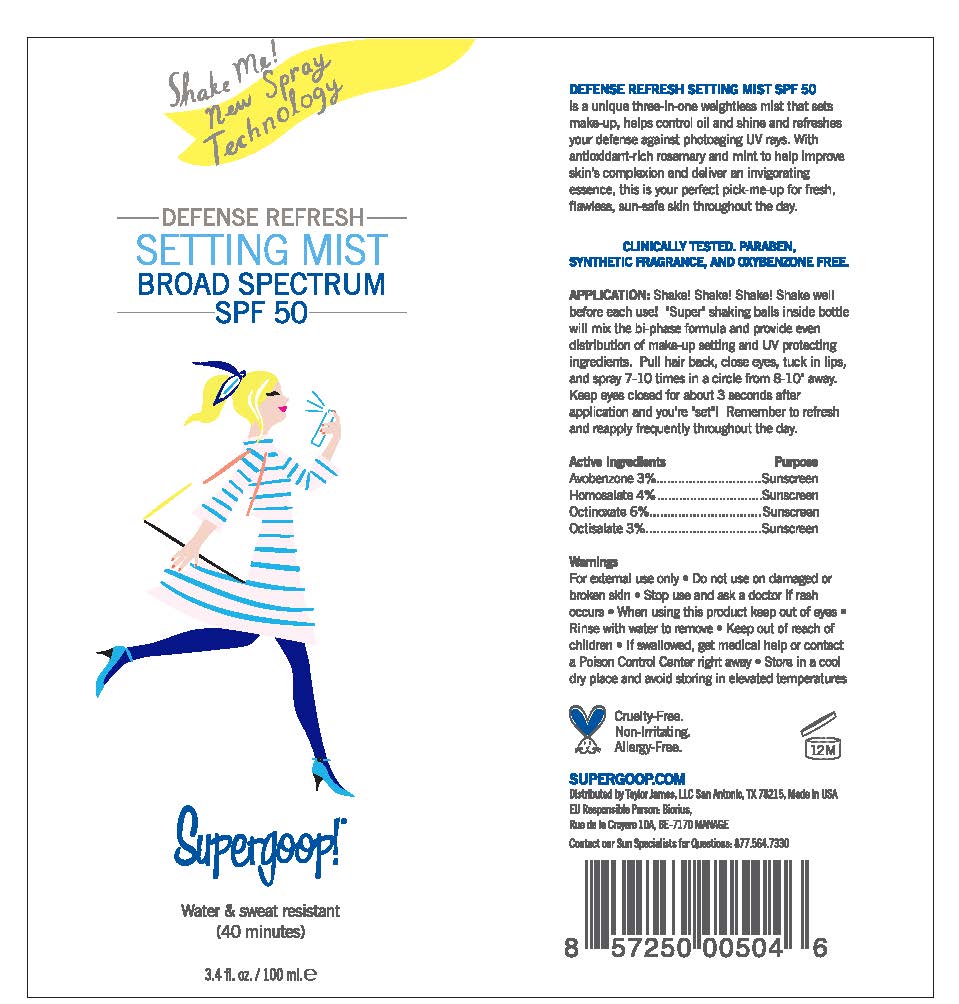 DRUG LABEL: Defense Refresh Settingh Mist Broad Spectrum Sunscreen SPF 50
NDC: 75936-133 | Form: LIQUID
Manufacturer: Taylor James, LTD
Category: otc | Type: HUMAN OTC DRUG LABEL
Date: 20170123

ACTIVE INGREDIENTS: AVOBENZONE 3 g/100 mL; HOMOSALATE 4 g/100 mL; OCTINOXATE 6 g/100 mL; OCTISALATE 3 g/100 mL
INACTIVE INGREDIENTS: ALCOHOL; BUTYLOCTYL SALICYLATE; MEDIUM-CHAIN TRIGLYCERIDES; DICAPRYLYL CARBONATE; ISODODECANE; PEPPERMINT OIL; SPEARMINT OIL; ROSEMARY OIL; WATER

Defense Refresh Setting Mist Broad Spectrum Sunscreen SPF 50

Active Ingredients Purpose

Avobenzone 3% Sunscreen

Homosalate 4% Sunscreen

Octinoxate 6% Sunscreen

Octisalate 3% Sunscreen

PURPOSE

Uses Helps prevent sunburn

If used as directed with other sun protection measures (see Directions), decreases the risk of skin cancer and early skin aging caused by the sun.

Keep out of reach of children

Stop use and ask a doctor if rash occurs

Warnings For external Use only

Do not use on damaged or broken skin

When using this product keep out of eyes

Rinse with water to remove

If swallowed, get medical help or contact a Poison Control Center right away

DOSAGE AND ADMINISTRATION

Directions Apply 15 minutes prior to sun exposure

Use a water resistant if swimming or sweating

Reapply at least every 2 hours

Children under 6 months: Ask a doctor

INACTIVE INGREDIENT

Inactive Ingredients Alcohol Denat., Caprylic Capric Triglyceride, Dicaprylyl Carbonate, Isododecane, Mentha Piperita (Peppermint) Stem/leaf Oil, Mentha Viridis (Spearmint) Leaf Oil, PVP, Rosmarinus Officinalis (Rosemary) Leaf Oil, Silica Silylate, WaterInactive Ingredients Alcohol Denat., Caprylic Capric Triglyceride, Dicaprylyl Carbonate, Isododecane, Mentha Piperita (Peppermint) Stem/leaf Oil, Mentha Viridis (Spearmint) Leaf Oil, PVP, Rosmarinus Officinalis (Rosemary) Leaf Oil, Silica Silylate, WaterInactive Ingredients Alcohol Denat., Caprylic Capric Triglyceride, Dicaprylyl Carbonate, Isododecane, Mentha Piperita (Peppermint) Stem/leaf Oil, Mentha Viridis (Spearmint) Leaf Oil, PVP, Rosmarinus Officinalis (Rosemary) Leaf Oil, Silica Silylate, Water

PACKAGE LABEL

Defense Refresh Setting Mist

With Rosemary

Broad Spectrum Sunscreen SPF 50

Matte finish three in one

sets make-up, controls oil and delivers UV photoaging protection